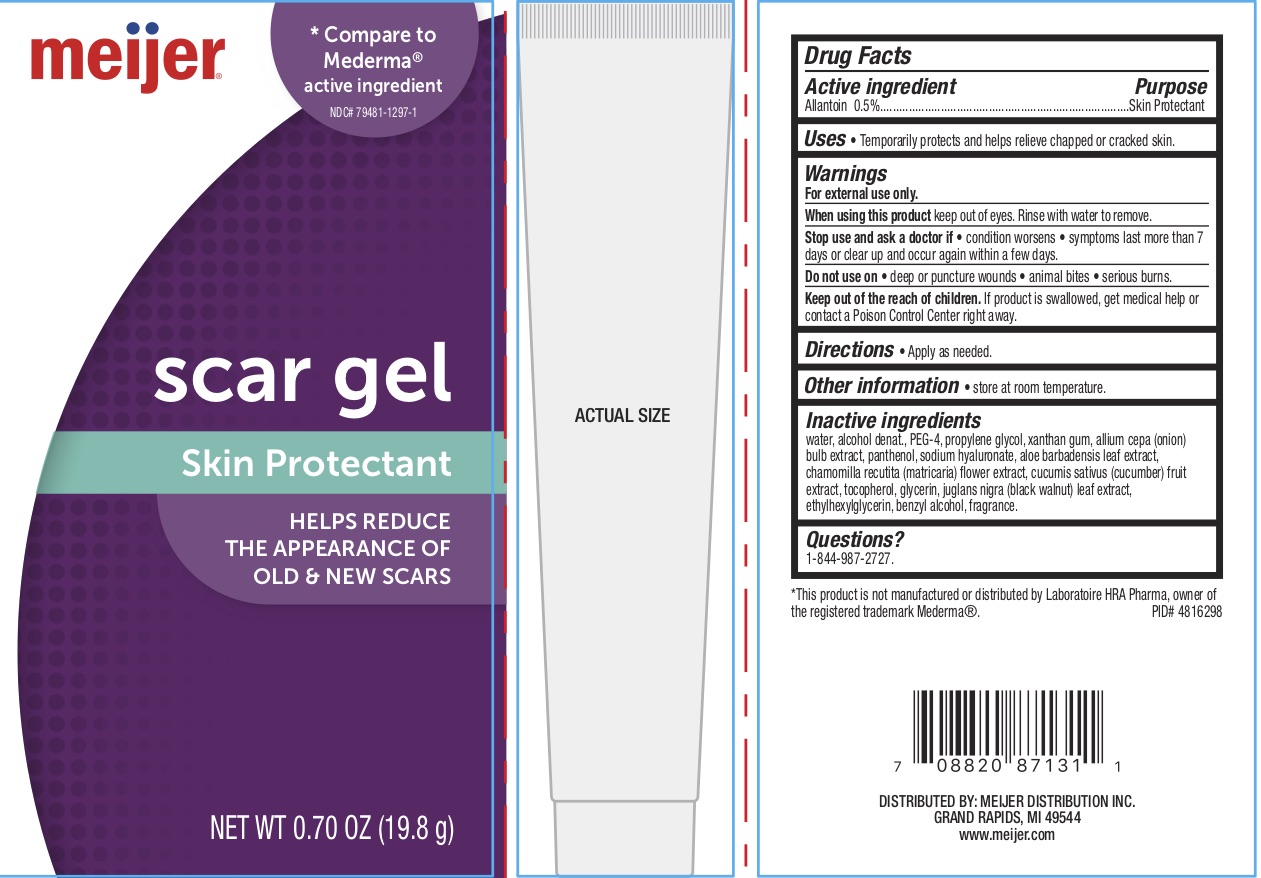 DRUG LABEL: Meijer Scar Gel
NDC: 79481-1297 | Form: GEL
Manufacturer: Meijer
Category: otc | Type: HUMAN OTC DRUG LABEL
Date: 20250206

ACTIVE INGREDIENTS: ALLANTOIN 0.5 g/100 g
INACTIVE INGREDIENTS: POLYETHYLENE GLYCOL 200; TOCOPHEROL; PANTHENOL; WATER; GLYCERIN; ONION; PROPYLENE GLYCOL; XANTHAN GUM; ALOE VERA LEAF; BLACK WALNUT; CHAMOMILE; CUCUMBER; ALCOHOL; ETHYLHEXYLGLYCERIN; BENZYL ALCOHOL; HYALURONATE SODIUM

Meijer Scar Gel

ACTIVE INGREDIENT

Allantoin 0.5%

PURPOSE

Skin Protectant.

DOSAGE AND ADMINISTRATION

Temporarily protects and helps relieve chapped or cracked skin.

WARNINGS

For external use only.

When using this product keep out of eyes. Rinse with water to remove.

Stop use and ask a doctor if the condition worsens or symptoms persist for more than 7 days or clear up and occur again within a few days.

Do not use on deep or puncture wounds, animal bites, and serious burns.

Keep out of reach of children. If the product is swallowed, get medical help or contact a Poison Control Center right away.

INDICATIONS AND USAGE

Apply as needed.

INACTIVE INGREDIENT

Water, Alcohol Denat., PEG-4, Propylene Glycol, Xanthan Gum, Allium Cepa (Onion) Bulk Extract, Panthenol, Sodium Hyaluronate, Aloe Barbadensis Leaf Extract, Chamomilla Recutita (Matricaria) Flower Extract, Cucumis Sativus (Cucumber) Fruit Extract, Tocopherol, Glycerin, Juglans Nigra (Black Walnut) Leaf Extract, Ethylhexylglycerin, Benzyl Alcohol, Fragrance.